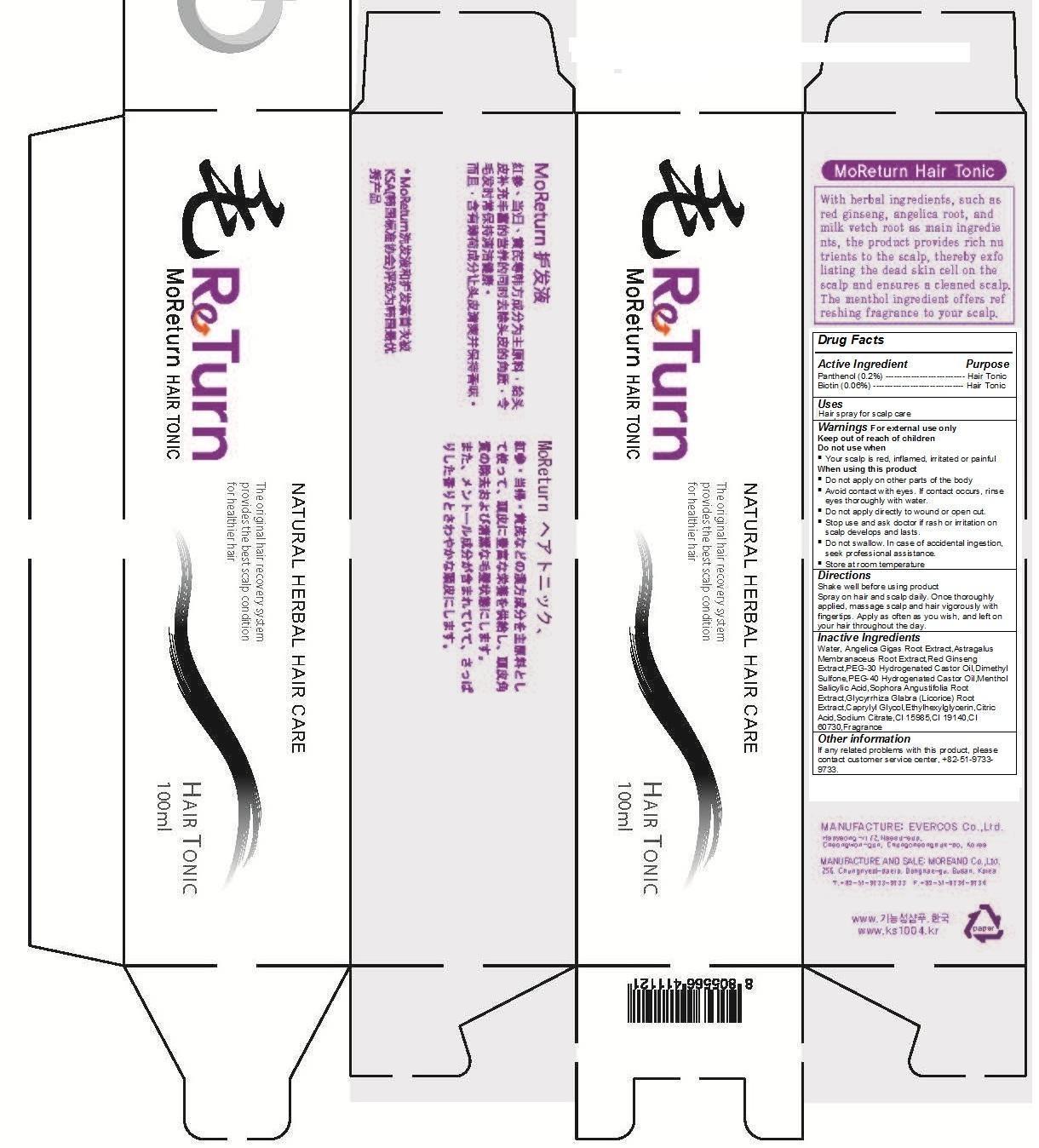 DRUG LABEL: MoReturn Hair Tonic
NDC: 61310-100 | Form: SPRAY
Manufacturer: Moreand Co., Ltd.
Category: otc | Type: HUMAN OTC DRUG LABEL
Date: 20131203

ACTIVE INGREDIENTS: PANTHENOL 0.2 g/100 mL; BIOTIN 0.06 g/100 mL
INACTIVE INGREDIENTS: WATER; ANGELICA GIGAS ROOT; ASTRAGALUS PROPINQUUS ROOT; ASIAN GINSENG; PEG-30 CASTOR OIL; DIMETHYL SULFONE; PEG-40 CASTOR OIL; MENTHOL; SALICYLIC ACID; SOPHORA FLAVESCENS ROOT; GLYCYRRHIZA GLABRA; CAPRYLYL GLYCOL; ETHYLHEXYLGLYCERIN; CITRIC ACID ACETATE; SODIUM CITRATE; FD&C YELLOW NO. 6; FD&C YELLOW NO. 5; EXT. D&C VIOLET NO. 2

MoReturn Hair Tonic

MoReturn Hair Tonic

Natural Herbal Hair Care

The original hair recovery system provides the best scalp condition for healthier hair.